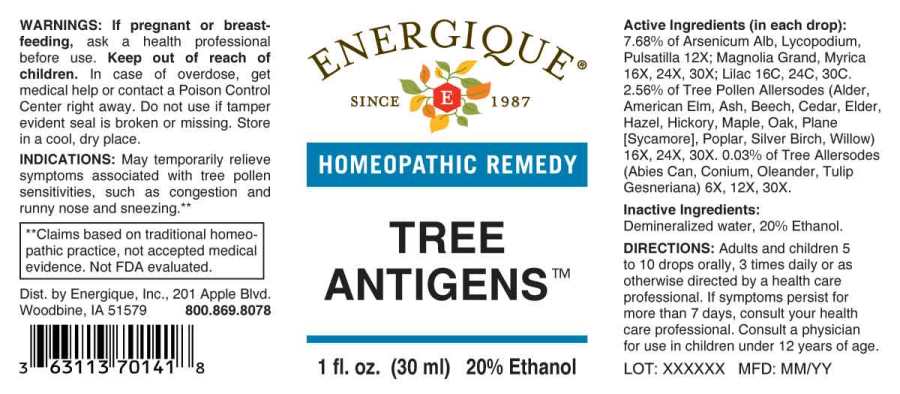 DRUG LABEL: Tree Antigens
NDC: 44911-0545 | Form: LIQUID
Manufacturer: Energique, Inc.
Category: homeopathic | Type: HUMAN OTC DRUG LABEL
Date: 20250519

ACTIVE INGREDIENTS: CONIUM MACULATUM FLOWERING TOP 6 [hp_X]/1 mL; TSUGA CANADENSIS BARK 6 [hp_X]/1 mL; TSUGA CANADENSIS FLOWER BUD 6 [hp_X]/1 mL; LIRIODENDRON TULIPIFERA WHOLE 6 [hp_X]/1 mL; NERIUM OLEANDER LEAF 6 [hp_X]/1 mL; ARSENIC TRIOXIDE 12 [hp_X]/1 mL; LYCOPODIUM CLAVATUM SPORE 12 [hp_X]/1 mL; PULSATILLA PRATENSIS WHOLE 12 [hp_X]/1 mL; MAGNOLIA GRANDIFLORA FLOWER 16 [hp_X]/1 mL; ULMUS GLABRA POLLEN 12 [hp_X]/1 mL; PLATANUS X ACERIFOLIA POLLEN 12 [hp_X]/1 mL; FRAXINUS EXCELSIOR POLLEN 12 [hp_X]/1 mL; FAGUS SYLVATICA POLLEN 12 [hp_X]/1 mL; SALIX X FRAGILIS POLLEN 12 [hp_X]/1 mL; SAMBUCUS CANADENSIS FLOWER 12 [hp_X]/1 mL; ALNUS RUBRA POLLEN 12 [hp_X]/1 mL; JUNIPERUS VIRGINIANA POLLEN 12 [hp_X]/1 mL; ACER SACCHARUM POLLEN 12 [hp_X]/1 mL; CORYLUS AVELLANA POLLEN 12 [hp_X]/1 mL; POPULUS ALBA POLLEN 12 [hp_X]/1 mL; BETULA PENDULA POLLEN 12 [hp_X]/1 mL; QUERCUS ROBUR POLLEN 12 [hp_X]/1 mL; CARYA GLABRA POLLEN 12 [hp_X]/1 mL; MORELLA CERIFERA ROOT BARK 16 [hp_X]/1 mL; SYRINGA VULGARIS FLOWER 16 [hp_C]/1 mL
INACTIVE INGREDIENTS: WATER; ALCOHOL

DRUG FACTS:

ACTIVE INGREDIENTS:

(in each drop): 7.68% of Arsenicum Album 12X, Lycopodium Clavatum 12X, Pulsatilla (Pratensis) 12X; Magnolia Grandiflora 16X, 24X, 30X, Myrica Cerifers 16X, 24X, 30X; Lilac (Syringa Vulgaris) 16C, 24C, 30C. 2.56% of Alder 16X, 24X, 30X, American Elm 16X, 24X, 30X, Ash 16X, 24X, 30X, Beech 16X, 24X, 30X, Cedar 16X, 24X, 30X, Elder (Box Elder) 16X, 24X, 30X, Hazel 16X, 24X, 30X, Hickory 16X, 24X, 30X, Maple 16X, 24X, 30X, Oak 16X, 24X, 30X, Plane (Sycamore) 16X, 24X, 30X, Poplar 16X, 24X, 30X, Silver Birch 16X, 24X, 30X, Willow 16X, 24X, 30X. 0.03% of Abies Canadensis 6X, 12X, 30X, Conium Maculatum 6X, 12X, 30X, Oleander 6X, 12X, 30X, Tulip Gesneriana 6X, 12X, 30X.

INDICATIONS:

May temporarily relieve symptoms associated with tree sensitivities, such as congestion and runny nose and sneezing.**

**Claims based on traditional homeopathic practice, not accepted medical evidence. Not FDA evalutated.

WARNINGS:

If pregnant or breastfeeding, ask a health professional before use.

Keep out of reach of children. In case of overdose, get medical help or contact a Poison Control Center right away.

Do not use if tamper evident seal is broken or missing.

Store in a cool, dry place.

Keep out of reach of children. In case of overdose, get medical help or contact a Poison Control Center right away.

DIRECTIONS:

Adults and children 5 to 10 drops orally, 3 times daily or as otherwise directed by a health care professional. If symptoms persist for more than 7 days, consult your health care professional. Consult a physician for use in children under 12 years of age.

INDICATIONS:

May temporarily relieve symptoms associated with tree sensitivities, such as congestion and runny nose and sneezing.**

**Claims based on traditional homeopathic practice, not accepted medical evidence. Not FDA evalutated.

INACTIVE INGREDIENTS:

Demineralized water, 20% Ethanol.

QUESTIONS:

Dist. by Energique, Inc.

201 Apple Blvd.

Woodbine, IA 51579 800.869.8078

PACKAGE LABEL DISPLAY:

ENERGIQUE

SINCE 1987

HOMEOPATHIC REMEDY

TREE

ANTIGENS

1 fl. oz. (30 ml)